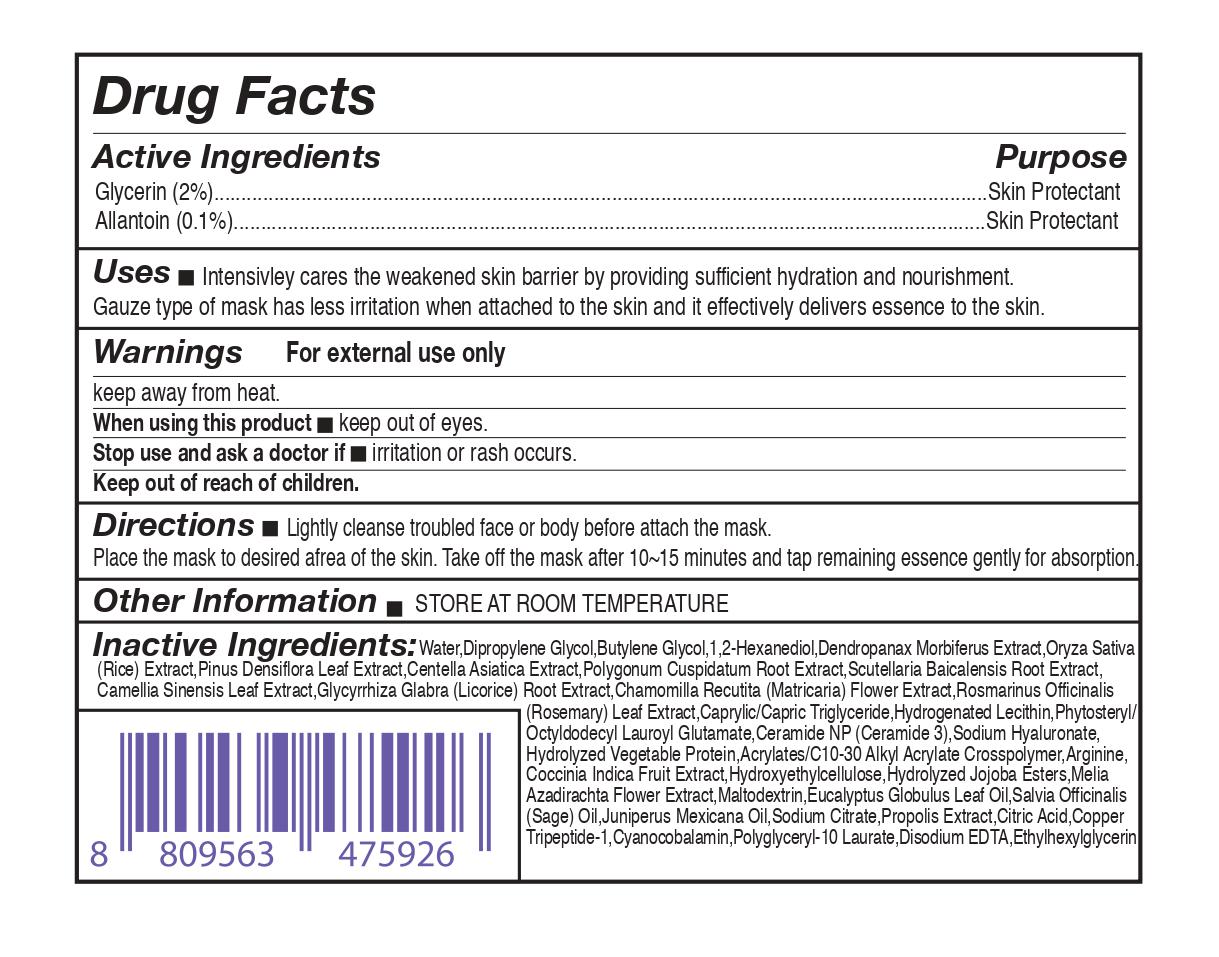 DRUG LABEL: repuera DermAtozyme 5% Gauze Dressing Mask
NDC: 81459-301 | Form: LIQUID
Manufacturer: ALLUV
Category: otc | Type: HUMAN OTC DRUG LABEL
Date: 20210128

ACTIVE INGREDIENTS: GLYCERIN 2 mg/100 mL; ALLANTOIN 0.1 mg/100 mL
INACTIVE INGREDIENTS: BUTYLENE GLYCOL; GERANIOL; LINALOOL, (+/-)-; CARBOMER INTERPOLYMER TYPE A (ALLYL SUCROSE CROSSLINKED); ARGININE; MALTODEXTRIN; POLYGLYCERYL-10 LAURATE; HYDROLYZED SOY PROTEIN (ENZYMATIC; 2000 MW); HYDROGENATED SOYBEAN LECITHIN; AZADIRACHTA INDICA FLOWER; SAGE OIL; EDETATE DISODIUM ANHYDROUS; ETHYLHEXYLGLYCERIN; CERAMIDE NP; RICE GERM; PINUS DENSIFLORA LEAF; CENTELLA ASIATICA; SCUTELLARIA BAICALENSIS ROOT; GLYCYRRHIZA GLABRA; ROSEMARY; MEDIUM-CHAIN TRIGLYCERIDES; COCCINIA GRANDIS LEAF; HYDROXYETHYL CELLULOSE, UNSPECIFIED; EUCALYPTUS OIL; JUNIPERUS DEPPEANA WOOD OIL; SODIUM CITRATE; PROPOLIS WAX; 1,2-HEXANEDIOL; LIMONENE, (+)-; WATER; PHYTOSTERYL/OCTYLDODECYL LAUROYL GLUTAMATE; HYDROLYZED JOJOBA ESTERS (ACID FORM); CITRIC ACID MONOHYDRATE; PREZATIDE COPPER; CYANOCOBALAMIN; DIPROPYLENE GLYCOL; POLYGONUM CUSPIDATUM ROOT; CHAMOMILE; GREEN TEA LEAF; HYALURONATE SODIUM

81459-301 re'puera DermAtozyme 5% Gauze Dressing Mask

Active Ingridients

Glycerin (2%)

Allantoin (0.1%)

Purpose

skin protectant

Uses

Intensivley cares the weakened skin barrier by providing sufficient hydration and nourishment.
Gauze type of mask has less irritation when attached to the skin and it effectively delivers essence to the skin.

Warnings

For external use only

keep away from heat.

When using this product

keep out of eyes.

Stop use and ask a doctor if

irritation or rash occurs.

Keep out of reach of children.

Directions

Lightly cleanse troubled face or body before attach the mask.
Place the mask to desired afrea of the skin. Take off the mask after 10~15 minutes and tap remaining essence gently for absorption.

Other Information

STORE AT ROOM TEMPERATURE

Inactive Ingredients

Water,Dipropylene Glycol ,Butylene Glycol, 1,2-Hexanediol,Dendropanax Morbiferus Extract,Oryza
Sativa (Rice) Extract,Pinus Densiflora Leaf Extract,Centella Asiatica Extract,Polygonum Cuspidatum Root Extract,Scutellaria Baicalensis Root
Extract,Camellia Sinensis Leaf Extract,Glycyrrhiza Glabra (Licorice) Root Extract,Chamomilla Recutita (Matricaria) Flower Extract,Rosmarinus
Officinalis (Rosemary) Leaf Extract,Caprylic/Capric Triglyceride,Hydrogenated Lecithin,
Phytosteryl/Octyldodecyl Lauroyl Glutamate,Ceramide NP (Ceramide 3),Sodium
Hyaluronate,Hydrolyzed Vegetable Protein,Acrylates/C10-30 Alkyl Acrylate
Crosspolymer,Arginine,Coccinia Indica Fruit Extract,Hydroxyethylcellulose,Hydrolyzed
Jojoba Esters,Melia Azadirachta Flower Extract,Maltodextrin ,Salvia Officinalis (Sage)
Oil,Eucalyptus Globulus Leaf Oil, Juniperus Mexicana Oil,Sodium Citrate,Propolis Extract,Citric Acid,Copper
Tripeptide-1,Cyanocobalamin,Polyglyceryl-10 Laurate,Disodium EDTA,Ethylhexylglycerin